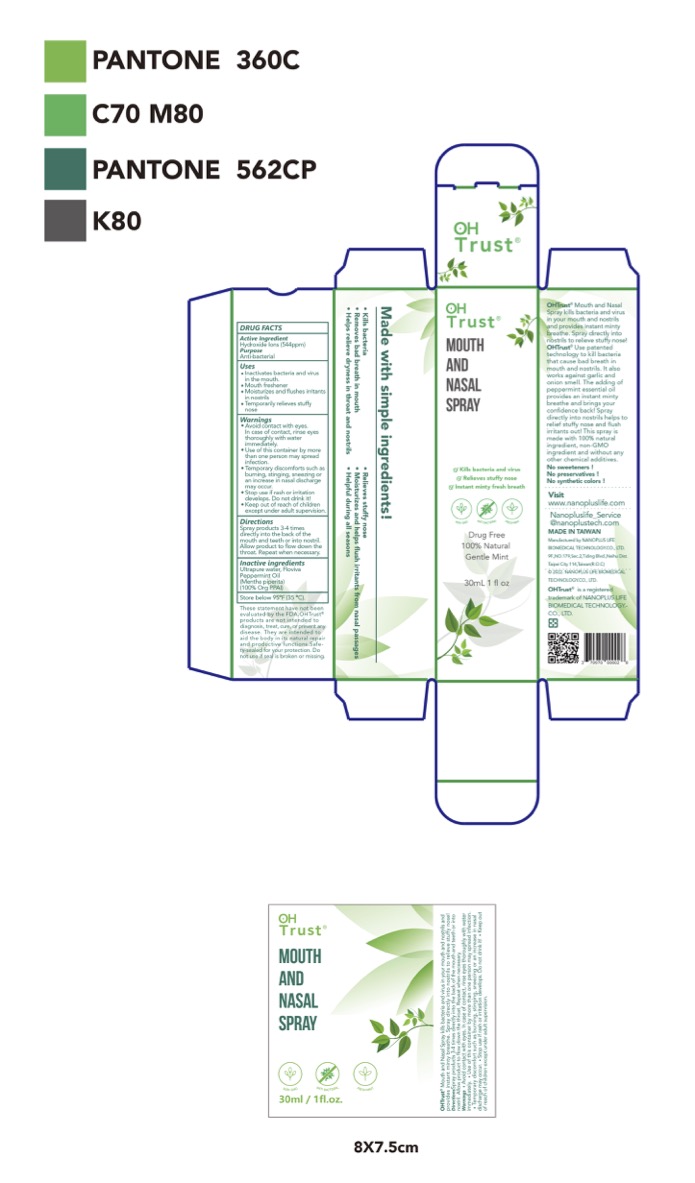 DRUG LABEL: OHTrust Mouth And Nasal Relief
NDC: 70970-007 | Form: LIQUID
Manufacturer: Nanoplus Limited (Cayman) Taiwan Branch
Category: otc | Type: HUMAN OTC DRUG LABEL
Date: 20250210

ACTIVE INGREDIENTS: HYDROXIDE ION 0.2 g/100 mL
INACTIVE INGREDIENTS: PEPPERMINT OIL; WATER

Nanoplus 007-01

Active Ingredient(s)

Hydroxide ions (544ppm)

Purpose

Anti-bacterial

Use

- For mouth:

Kills bacteria and virus
Balance pH
Instant minty breath

- For nasal:

Moisturizes and flushes irritants in nostrils

Relieves stuffy nose

Warnings

- Avoid contact with eyes. In case of contact, rinse eyes thoroughly with water immediately.
- Use of this container by more than one person may spread infection.
- Temporary discomforts such as burning, stinging, sneezing or an increase in nasal discharge may occur.
- Stop use if rash or irritation develops. Do not drink it!

Keep out of reach of children except under adult supervision.

Directions

Spray products 3-4 times directly into the back of the mouth and teeth or into nostril. Allow product to flow down the throat. Repeat when necessary.

Other information

Store below 95˚F (35˚C).

Inactive ingredients

Ultrapure water, Floviva Peppermint Oil (Mentha piperita) (100% Org PPAI)

Package Label - Principal Display Panel

30 mL NDC: 70970-007-01